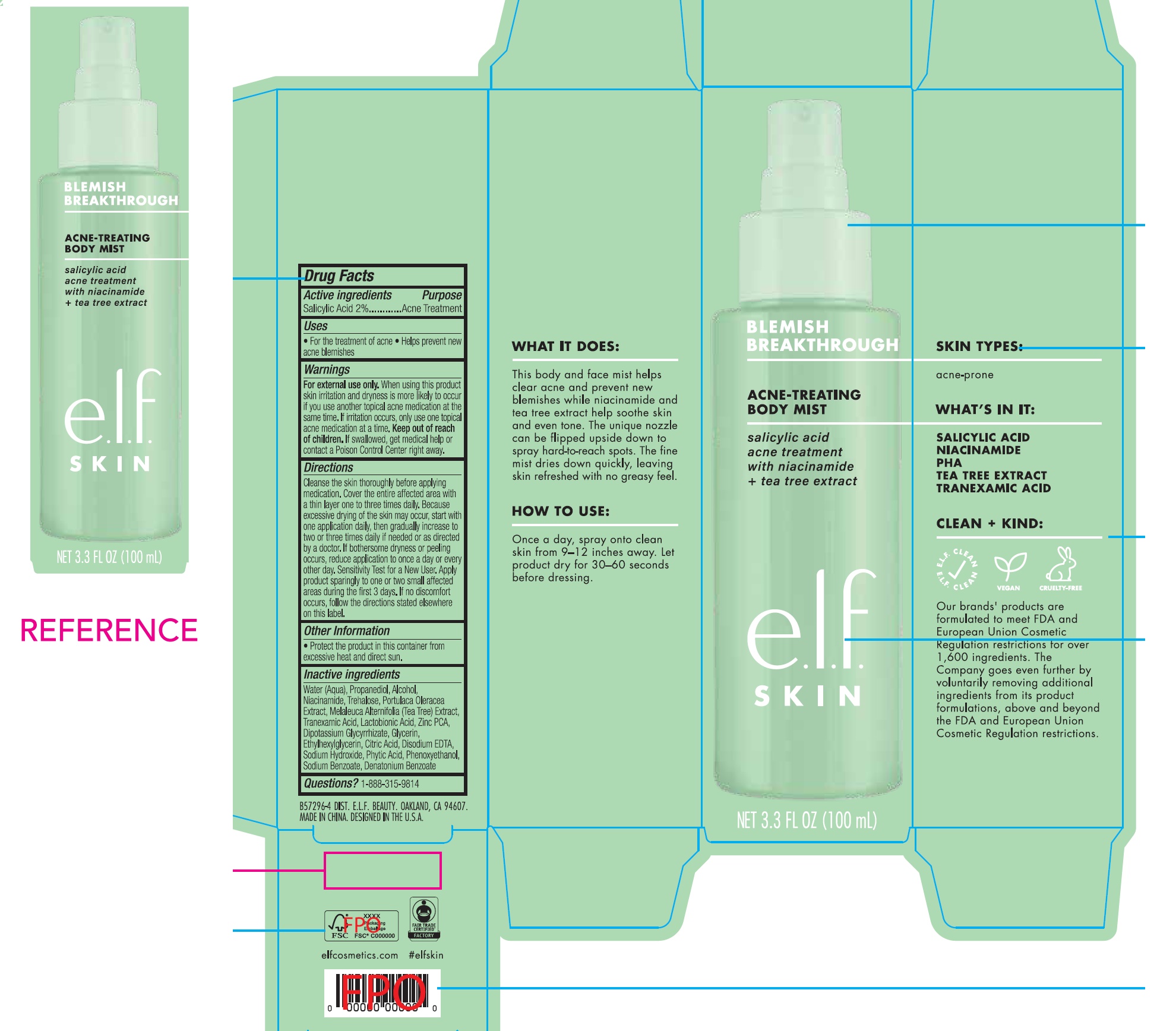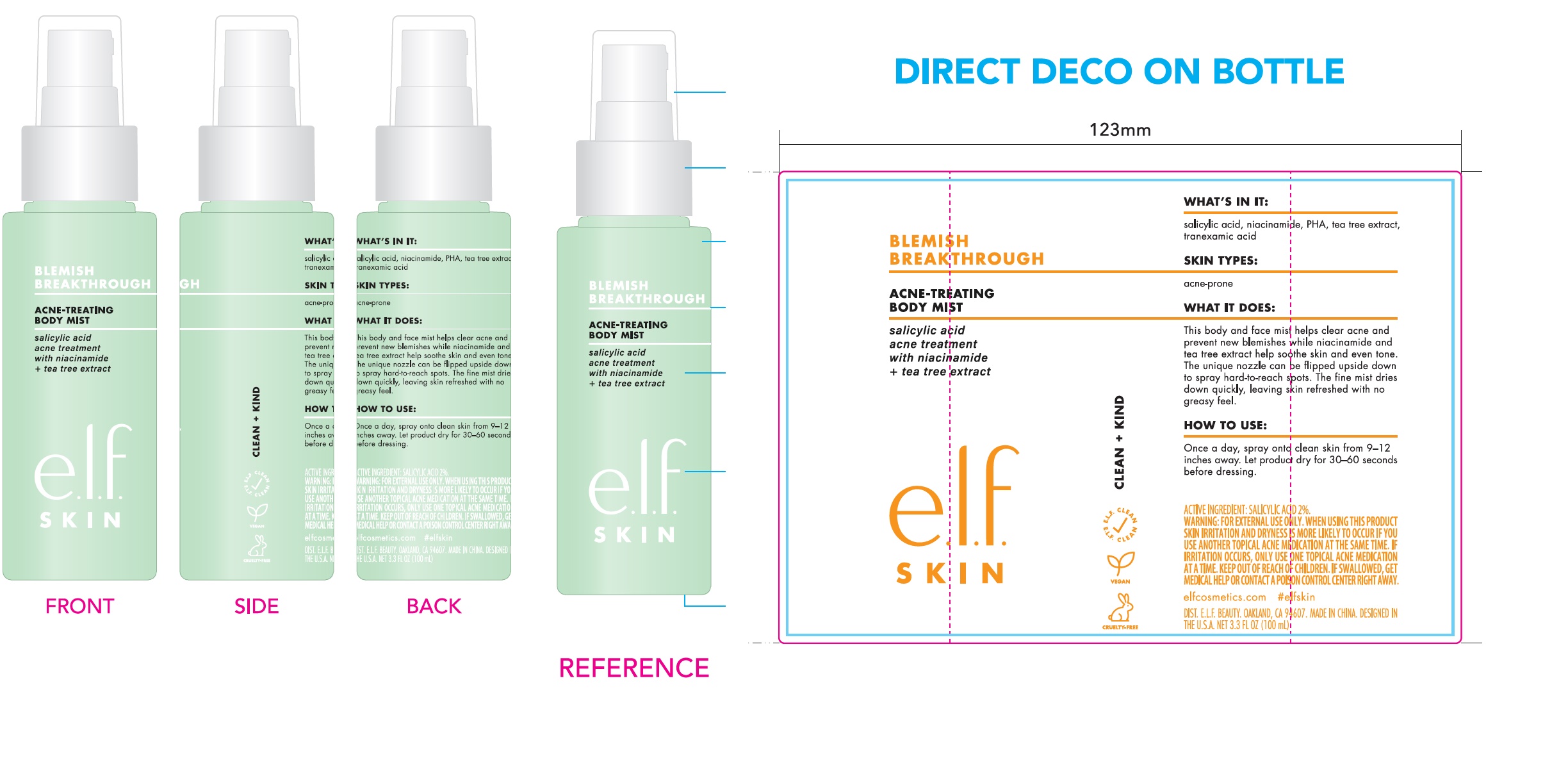 DRUG LABEL: e.l.f Skin Acne-Treating Body Mist
NDC: 76354-418 | Form: LIQUID
Manufacturer: e.l.f. Cosmetics, Inc
Category: otc | Type: HUMAN OTC DRUG LABEL
Date: 20251107

ACTIVE INGREDIENTS: SALICYLIC ACID 20 mg/1 mL
INACTIVE INGREDIENTS: PROPANEDIOL; ALCOHOL; NIACINAMIDE; WATER; TREHALOSE; PURSLANE; MELALEUCA ALTERNIFOLIA LEAF; TRANEXAMIC ACID; LACTOBIONIC ACID; ZINC PIDOLATE; GLYCYRRHIZINATE DIPOTASSIUM; GLYCERIN; ETHYLHEXYLGLYCERIN; CITRIC ACID MONOHYDRATE; EDETATE DISODIUM ANHYDROUS; SODIUM HYDROXIDE; FYTIC ACID; PHENOXYETHANOL; SODIUM BENZOATE; DENATONIUM BENZOATE

e.l.f Skin Acne-Treating Body Mist

Active ingredients

Salicylic Acid 2%

Purpose

Acne Treatment

Uses

- For the treatment of acne
- Helps prevent new acne blemishes

Warnings

For external use only,

When using this product

skin irritation and dryness is more likely to occur if you use another topical acne medication at the same time. If irritation occurs, only use one topical acne medication at a time.

Keep out of reach of children.

If swallowed, get medical help or contact a Poison Control Center right away.

Directions

Cleanse the skin thoroughly before applying medication. Cover the entire affected area with a thin layer one to three times daily. Because excessive drying of the skin may occur, start with one application daily, then gradually increase to two or three times daily if needed or as directed by a doctor. If bothersome dryness or peeling occurs, reduce application to once a day or every other day. Sensitivity Test for a New User. Apply product sparingly to one or two small affected areas during the first 3 days. If no discomfort occurs, follow the directions stated elsewhere on this label.

Inactive ingredients

Water (Aqu), Propanediol, Alcohol, Niacinamide, Trehalose, Portulaca Oleracea Extract, Melaleuca Alternifolia (Tea Tree) Extract, Tranexamic Acid, Lactobionic Acid, Zinc PCA, Dipotassium Glycyrrhizate, Glycerin, Ethylhexylglycerin, Citric Acid, Disodium EDTA, Sodium Hydroxide, Phytic Acid, Phenoxyethanol, Sodium Benzoate, Denatonium Benzoate

Questions?

1-888-315-9814